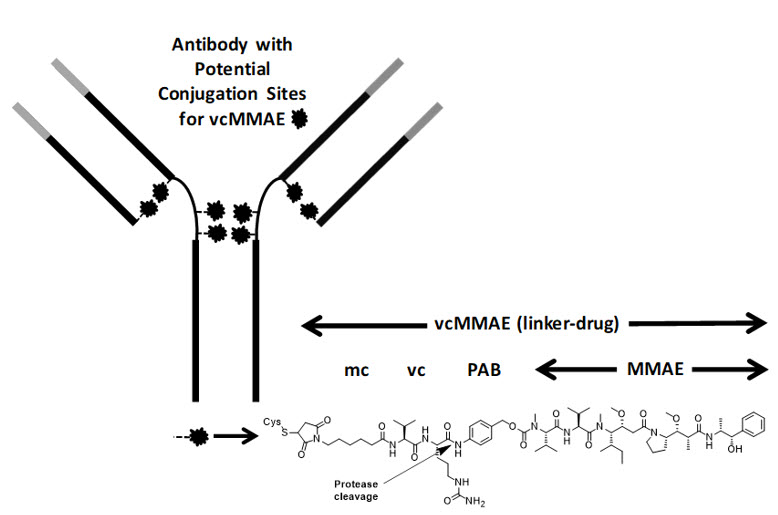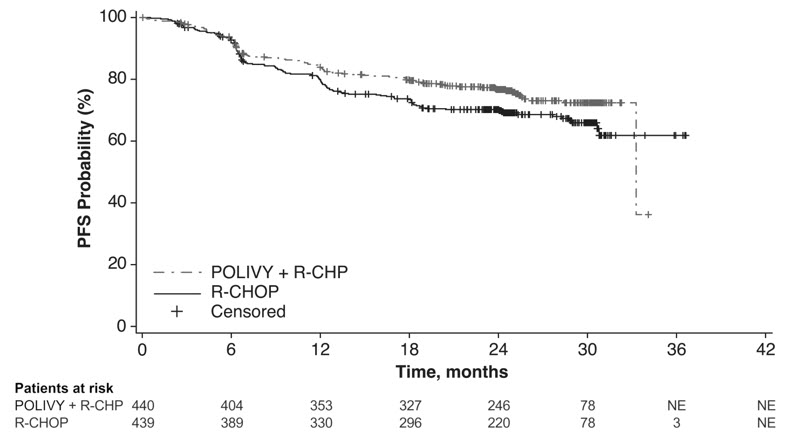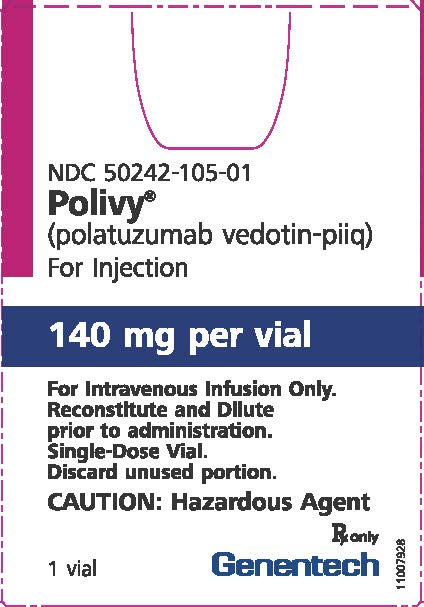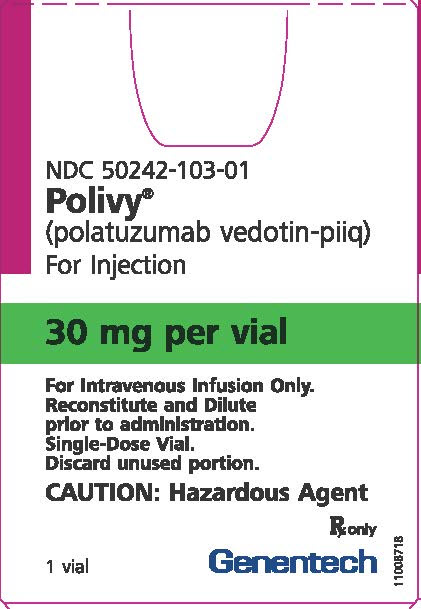 DRUG LABEL: POLIVY
NDC: 50242-105 | Form: INJECTION, POWDER, LYOPHILIZED, FOR SOLUTION
Manufacturer: Genentech, Inc.
Category: prescription | Type: HUMAN PRESCRIPTION DRUG LABEL
Date: 20251202

ACTIVE INGREDIENTS: POLATUZUMAB VEDOTIN 140 mg/7.52 mL
INACTIVE INGREDIENTS: SUCCINIC ACID 8.27 mg/7.52 mL; SODIUM HYDROXIDE 3.8 mg/7.52 mL; SUCROSE 288 mg/7.52 mL; POLYSORBATE 20 8.4 mg/7.52 mL

HIGHLIGHTS OF PRESCRIBING INFORMATION

These highlights do not include all the information needed to use POLIVY safely and effectively. See full prescribing information for POLIVY.
POLIVY® (polatuzumab vedotin-piiq) for injection, for intravenous use
Initial U.S. Approval: 2019

RECENT MAJOR CHANGES

Indications and Usage (1.1, 1.2) | 4/2023
Dosage and Administration (2.1. 2.2, 2.3, 2.4) | 4/2023
Warnings and Precautions (5.1, 5.2. 5.3, 5.4, 5.7) | 4/2023

1 INDICATIONS AND USAGE

POLIVY is a CD79b-directed antibody and microtubule inhibitor conjugate indicated:

- in combination with a rituximab product, cyclophosphamide, doxorubicin, and prednisone (R-CHP) for the treatment of adult patients who have previously untreated diffuse large B-cell lymphoma (DLBCL), not otherwise specified (NOS) or high-grade B-cell lymphoma (HGBL) and who have an International Prognostic Index score of 2 or greater. (1.1)
- in combination with bendamustine and a rituximab product for the treatment of adult patients with relapsed or refractory DLBCL, NOS, after at least two prior therapies. (1.2)

2 DOSAGE AND ADMINISTRATION

- The recommended dose of POLIVY is 1.8 mg/kg as an intravenous infusion every 21 days for 6 cycles. (2)
- Administer the initial POLIVY dose over 90 minutes. Subsequent infusions may be administered over 30 minutes if the previous infusion is tolerated. (2)
- Premedicate with an antihistamine and antipyretic before POLIVY. (2)
- See Full Prescribing Information for instructions on preparation and administration. (2.4)

3 DOSAGE FORMS AND STRENGTHS

For injection: 30 mg or 140 mg of polatuzumab vedotin-piiq as a lyophilized powder in a single-dose vial. (3)

4 CONTRAINDICATIONS

None. (4)

5 WARNINGS AND PRECAUTIONS

- Peripheral Neuropathy: Monitor patients for peripheral neuropathy and modify or discontinue dose accordingly. (5.1)
- Infusion-Related Reactions: Premedicate with an antihistamine and antipyretic. Monitor patients closely during infusions. Interrupt or discontinue infusion for reactions. (5.2)
- Myelosuppression: Monitor complete blood counts. Manage using dose delays or reductions and growth factor support. Monitor for signs of infection. (5.3)
- Serious and Opportunistic Infections: Closely monitor patients for signs of bacterial, fungal, or viral infections. (5.4)
- Progressive Multifocal Leukoencephalopathy (PML): Monitor patients for new or worsening neurological, cognitive, or behavioral changes suggestive of PML. (5.5)
- Tumor Lysis Syndrome: Closely monitor patients with high tumor burden or rapidly proliferative tumors. (5.6)
- Hepatotoxicity: Monitor liver enzymes and bilirubin. (5.7)
- Embryo-Fetal Toxicity: Can cause fetal harm. Advise females of reproductive potential of the potential risk to a fetus and to use effective contraception during treatment and for 3 months after the last dose. (5.8)

6 ADVERSE REACTIONS

The most common adverse reactions (≥20%) in patients with large B-cell lymphoma treated with POLIVY in combination with R-CHP, excluding laboratory abnormalities, are peripheral neuropathy, nausea, fatigue, diarrhea, constipation, alopecia, and mucositis. Grade 3 to 4 laboratory abnormalities (≥10%) are lymphopenia, neutropenia, hyperuricemia, and anemia. (6.1)

The most common adverse reaction (≥20%) in patients with relapsed or refractory DLBCL treated with POLIVY in combination with BR are neutropenia, thrombocytopenia, anemia, peripheral neuropathy, fatigue, diarrhea, pyrexia, decreased appetite, and pneumonia. (6.1)

To report SUSPECTED ADVERSE REACTIONS, contact Genentech at 1-888-835-2555 or FDA at 1-800-FDA-1088 or www.fda.gov/medwatch.

7 DRUG INTERACTIONS

Concomitant use of strong CYP3A inhibitors or inducers has the potential to affect the exposure to unconjugated monomethyl auristatin E (MMAE). (7.1)

8 USE IN SPECIFIC POPULATIONS

- Hepatic impairment has the potential to increase exposure to MMAE. Monitor patients for adverse reactions. (8.6)
- Lactation: Advise not to breastfeed. (8.2)

FULL PRESCRIBING INFORMATION

1 INDICATIONS AND USAGE

1.1 Previously Untreated DLBCL, NOS or HGBL

POLIVY in combination with a rituximab product, cyclophosphamide, doxorubicin, and prednisone (R-CHP) is indicated for the treatment of adult patients who have previously untreated diffuse large B-cell lymphoma (DLBCL), not otherwise specified (NOS) or high-grade B-cell lymphoma (HGBL) and who have an International Prognostic Index score of 2 or greater.

1.2 Relapsed or Refractory DLBCL, NOS

POLIVY in combination with bendamustine and a rituximab product is indicated for the treatment of adult patients with relapsed or refractory DLBCL, NOS, after at least two prior therapies.

2 DOSAGE AND ADMINISTRATION

2.1 Recommended Dosage

Patients with Previously Untreated DLBCL, NOS or HGBL

The recommended dosage of POLIVY is 1.8 mg/kg administered as an intravenous infusion every 21 days for 6 cycles in combination with a rituximab product, cyclophosphamide, doxorubicin, and prednisone [see Clinical Studies (14.1)]. Administer POLIVY, cyclophosphamide, doxorubicin, and a rituximab product in any order on Day 1 after the administration of prednisone. Prednisone is administered on Days 1–5 of each cycle.

Patients with Relapsed or Refractory DLBCL, NOS

The recommended dosage of POLIVY is 1.8 mg/kg administered as an intravenous infusion every 21 days for 6 cycles in combination with bendamustine and a rituximab product. Administer POLIVY, bendamustine, and a rituximab product in any order on Day 1 of each cycle. The recommended dose of bendamustine is 90 mg/m^2/day on Days 1 and 2 when administered with POLIVY and a rituximab product. The recommended dose of rituximab product is 375 mg/m^2 intravenously on Day 1 of each cycle.

For All Indicated Patients

If not already premedicated, administer an antihistamine and antipyretic at least 30 minutes prior to POLIVY.

If a planned dose of POLIVY is missed, administer as soon as possible. Adjust the schedule of administration to maintain a 21-day interval between doses.

2.2 Management of Adverse Reactions

Previously Untreated DLBCL, NOS or HGBL

Table 1 provides management guidelines for peripheral neuropathy in patients receiving POLIVY plus R-CHP [see Warnings and Precautions (5.1)].

Table 1 Management of Peripheral Neuropathy in Patients Receiving POLIVY Plus R-CHP
Adverse reaction | Grade | Dose modification [Starting dose for POLIVY is 1.8 mg/kg. First dose reduction level is 1.4 mg/kg. Second dose reduction level is 1 mg/kg. No further dose reduction is recommended beyond 1 mg/kg. If further reduction needed discontinue POLIVY.]
Peripheral sensory neuropathy | Grade 1 | None
Peripheral sensory neuropathy | Grade 2 | If resolves to Grade 1 or lower before the next scheduled dose, resume at the same dose level. If Gr 2 persists at the next scheduled dose, reduce one dose level.
Peripheral sensory neuropathy | Grade 3 | Withhold until Grade 2 or lower and reduce one dose level.
Peripheral sensory neuropathy | Grade 4 | Permanently discontinue.
Peripheral motor neuropathy | Grade 1 | None
Peripheral motor neuropathy | Grade 2 or 3 | Withhold until Grade 1 or lower and reduce one dose level.
Peripheral motor neuropathy | Grade 4 | Permanently discontinue.
R-CHP should be continued if POLIVY is withheld.
If there is concurrent sensory and motor neuropathy, follow the guidance for the most severe neuropathy. If the grade of sensory and motor neuropathy are the same, follow the guidance for motor neuropathy.

Table 2 provides management guidelines for infusion-related reaction and myelosuppression [see Warnings and Precautions (5.2 and 5.3)].

Table 2 Management of Infusion-Related Reaction and Myelosuppression in Patients Receiving POLIVY Plus R-CHP
Adverse Reaction | Dosage Modification [Starting dose for POLIVY is 1.8 mg/kg. First dose reduction level is 1.4 mg/kg. Second dose reduction level is 1 mg/kg. No further dose reduction is recommended beyond 1 mg/kg. If further reduction needed discontinue POLIVY.]
Infusion-Related Reaction Grade 1–3 | Interrupt POLIVY infusion and give supportive treatment. For the first instance of Grade 3 wheezing, bronchospasm, or generalized urticaria, permanently discontinue POLIVY. For recurrent Grade 2 wheezing or urticaria, or for recurrence of any Grade 3 symptoms, permanently discontinue POLIVY. Otherwise, upon complete resolution of symptoms, infusion may be resumed at 50% of the rate achieved prior to interruption. In the absence of infusion related symptoms, the rate of infusion may be escalated in increments of 50 mg/hour every 30 minutes. For the next cycle, infuse POLIVY over 90 minutes. If no infusion-related reaction occurs, subsequent infusions may be administered over 30 minutes. Administer premedication for all cycles.
Infusion-Related Reaction Grade 4 | Stop POLIVY infusion immediately. Give supportive treatment. Discontinue POLIVY.
Neutropenia [Severity on Day 1 of any cycle.] , [If primary cause is lymphoma, dosage delay or reduction may not be needed.] Grade 3–4 | Hold all treatment until ANC recovers to greater than or equal to 1,000/microliter. Consider therapeutic G-CSF if neutropenia occurs after prophylactic G-CSF. If ANC recovers to greater than or equal to 1,000/microliter on or before Day 7, resume all treatment without any dose reductions. If ANC recovers to greater than or equal to 1,000/microliter after Day 7:; - resume all treatment - administer prophylactic G-CSF in next cycle. If G-CSF was already given, consider a dose reduction of POLIVY.
Thrombocytopenia, Grade 3–4 | Hold all treatment until platelets recover to greater than or equal to 75,000/microliter. If platelets recover to greater than or equal to 75,000/microliter on or before Day 7, resume all treatment without any dose reductions. If platelets recover to greater than or equal to 75,000/microliter after Day 7:; - resume all treatment and consider a dose reduction of POLIVY.
Toxicity graded per National Cancer Institute (NCI) Common Terminology for Adverse Events (CTCAE) version 4.0.

Relapsed or Refractory DLBCL, NOS

Table 3 provides management guidelines for peripheral neuropathy, infusion-related reaction, and myelosuppression in patients receiving POLIVY in combination with bendamustine and a rituximab product [see Warnings and Precautions (5.1, 5.2, 5.3)].

Table 3 Management of Peripheral Neuropathy, Infusion-Related Reaction, and Myelosuppression in Patients Receiving POLIVY Plus Bendamustine and a Rituximab Product
Adverse Reaction | Dosage Modification [Starting dose for POLIVY is 1.8 mg/kg. First dose reduction level is 1.4 mg/kg. Second dose reduction level is 1 mg/kg. No further dose reduction is recommended beyond 1 mg/kg. If further reduction needed discontinue POLIVY.]
Peripheral Neuropathy Grade 2–3 | Hold POLIVY dosing until improvement to Grade 1 or lower. If recovered to Grade 1 or lower on or before Day 14, restart POLIVY with the next cycle at a permanently reduced dose of 1.4 mg/kg. If a prior dose reduction to 1.4 mg/kg has occurred, discontinue POLIVY. If not recovered to Grade 1 or lower on or before Day 14, discontinue POLIVY.
Peripheral Neuropathy Grade 4 | Discontinue POLIVY.
Infusion-Related Reaction Grade 1–3 | Interrupt POLIVY infusion and give supportive treatment. For the first instance of Grade 3 wheezing, bronchospasm, or generalized urticaria, permanently discontinue POLIVY. For recurrent Grade 2 wheezing or urticaria, or for recurrence of any Grade 3 symptoms, permanently discontinue POLIVY. Otherwise, upon complete resolution of symptoms, infusion may be resumed at 50% of the rate achieved prior to interruption. In the absence of infusion related symptoms, the rate of infusion may be escalated in increments of 50 mg/hour every 30 minutes. For the next cycle, infuse POLIVY over 90 minutes. If no infusion-related reaction occurs, subsequent infusions may be administered over 30 minutes. Administer premedication for all cycles.
Infusion-Related Reaction Grade 4 | Stop POLIVY infusion immediately. Give supportive treatment. Permanently discontinue POLIVY.
Neutropenia [Severity on Day 1 of any cycle.] , [If primary cause is lymphoma, dosage delay or reduction may not be needed.] Grade 3–4 | Hold all treatment until ANC recovers to greater than 1,000/microliter. If ANC recovers to greater than 1,000/microliter on or before Day 7, resume all treatment without any additional dose reductions. Consider granulocyte colony-stimulating factor prophylaxis for subsequent cycles, if not previously given. If ANC recovers to greater than 1,000/microliter after Day 7:; - restart all treatment. Consider granulocyte colony-stimulating factor prophylaxis for subsequent cycles, if not previously given. If prophylaxis was given, consider dose reduction of bendamustine. - if dose reduction of bendamustine has already occurred, consider dose reduction of POLIVY to 1.4 mg/kg.
Thrombocytopenia, Grade 3–4 | Hold all treatment until platelets recover to greater than 75,000/microliter. If platelets recover to greater than 75,000/microliter on or before Day 7, resume all treatment without any additional dose reductions. If platelets recover to greater than 75,000/microliter after Day 7:; - restart all treatment, with dose reduction of bendamustine. - if dose reduction of bendamustine has already occurred, consider dose reduction of POLIVY to 1.4 mg/kg.
Toxicity graded per NCI CTCAE version 4.0.

2.3 Recommended Prophylactic Medications

If not already premedicated for a rituximab product, administer an antihistamine and antipyretic at least 30 to 60 minutes prior to POLIVY for potential infusion-related reactions [see Warnings and Precautions (5.2)].

Administer prophylaxis for Pneumocystis jiroveci pneumonia and herpesvirus throughout treatment with POLIVY.

Administer prophylactic granulocyte colony-stimulating factor (G-CSF) for neutropenia in patients receiving POLIVY plus R-CHP. Consider prophylactic G-CSF administration for neutropenia in patients receiving POLIVY plus bendamustine and a rituximab product [see Warnings and Precautions (5.3)].

Administer tumor lysis syndrome prophylaxis for patients at increased risk of tumor lysis syndrome [see Warnings and Precautions (5.6)].

2.4 Instructions for Preparation and Administration

Reconstitute and further dilute POLIVY prior to intravenous infusion.

POLIVY is a hazardous drug. Follow applicable special handling and disposal procedures.^1

Parenteral drug products should be inspected visually for particulate matter and discoloration prior to administration, whenever solution and container permit.

Reconstitution

- Reconstitute immediately before dilution.
- More than one vial may be needed for a full dose. Calculate the dose, the total volume of reconstituted POLIVY solution required, and the number of POLIVY vials needed.
- Using a sterile syringe, slowly inject Sterile Water for Injection, USP, using the volume provided in Table 4, into the POLIVY vial, with the stream directed toward the inside wall of the vial to obtain a concentration of 20 mg/mL of polatuzumab vedotin-piiq.

Table 4 Reconstitution Volumes
Strength | Volume of Sterile Water for Injection, USP required for reconstitution
30 mg vial | 1.8 mL
140 mg vial | 7.2 mL

- Swirl the vial gently until completely dissolved. Do not shake.
- Inspect the reconstituted solution for discoloration and particulate matter. The reconstituted solution should appear colorless to slightly brown, clear to slightly opalescent, and free of visible particulates. Do not use if the reconstituted solution is discolored, is cloudy, or contains visible particulates. Do not freeze or expose to direct sunlight.
- If needed, store unused reconstituted POLIVY solution refrigerated at 2°C to 8°C (36°F to 46°F) for up to 48 hours or at room temperature (9°C to 25°C, 47°F to 77°F) up to a maximum of 8 hours prior to dilution. Discard vial when cumulative storage time prior to dilution exceeds 48 hours.

Dilution

- Dilute polatuzumab vedotin-piiq to a final concentration of 0.72–2.7 mg/mL in an intravenous infusion bag with a minimum volume of 50 mL containing 0.9% Sodium Chloride Injection, USP, 0.45% Sodium Chloride Injection, USP, or 5% Dextrose Injection, USP.
- Determine the volume of 20 mg/mL reconstituted solution needed based on the required dose.
- Withdraw the required volume of reconstituted solution from the POLIVY vial using a sterile syringe and dilute into the intravenous infusion bag. Discard any unused portion left in the vial.
- Gently mix the intravenous bag by slowly inverting the bag. Do not shake.
- Inspect the intravenous bag for particulates and discard if present.
- If not used immediately, store the diluted POLIVY solution as specified in Table 5. Discard if storage time exceeds these limits. Do not freeze or expose to direct sunlight.

Table 5 Diluted POLIVY Solution Storage Conditions
Diluent Used to Prepare Solution for Infusion | Diluted POLIVY Solution Storage Conditions [To ensure product stability, do not exceed specified storage durations.]
0.9% Sodium Chloride Injection, USP | Up to 36 hours at 2°C to 8°C (36°F to 46°F) or up to 4 hours at room temperature (9 to 25°C, 47 to 77°F)
0.45% Sodium Chloride Injection, USP | Up to 18 hours at 2°C to 8°C (36°F to 46°F) or up to 4 hours at room temperature (9 to 25°C, 47 to 77°F)
5% Dextrose Injection, USP | Up to 36 hours at 2°C to 8°C (36°F to 46°F) or up to 6 hours at room temperature (9 to 25°C, 47 to 77°F)

- Limit transportation to 30 minutes at 9°C to 25°C or 24 hours at 2°C to 8°C (refer to instructions below). The total storage plus transportation times of the diluted product should not exceed the storage duration specified in Table 5.
- Agitation stress can result in aggregation. Limit agitation of diluted product during preparation and transportation to administration site. Do not transport diluted product through an automated system (e.g., pneumatic tube or automated cart). If the prepared solution will be transported to a separate facility, remove air from the infusion bag to prevent aggregation. If air is removed, an infusion set with a vented spike is required to ensure accurate dosing during the infusion.
- No incompatibilities have been observed between POLIVY and intravenous infusion bags with product-contacting materials of polyvinyl chloride (PVC) or polyolefins (PO) such as polyethylene (PE) and polypropylene (PP). No incompatibilities have been observed with infusion sets or infusion aids with product-contacting materials of PVC, PE, polyurethane (PU), polybutadiene (PBD), acrylonitrile butadiene styrene (ABS), polycarbonate (PC), polyetherurethane (PEU), fluorinated ethylene propylene (FEP), or polytetrafluorethylene (PTFE), or with filter membranes composed of polyether sulfone (PES) or polysulfone (PSU).

Administration

- Administer POLIVY as an intravenous infusion only.
- Administer the initial dose of POLIVY over 90 minutes. Monitor patients for infusion-related reactions during the infusion and for a minimum of 90 minutes following completion of the initial dose. If the previous infusion was well tolerated, the subsequent dose of POLIVY may be administered as a 30-minute infusion and patients should be monitored during the infusion and for at least 30 minutes after completion of the infusion.
- POLIVY must be administered using a dedicated infusion line equipped with a sterile, non-pyrogenic, low-protein-binding in-line or add-on filter (0.2- or 0.22-micron pore size) and a catheter.
- Do not mix POLIVY with or administer as an infusion with other drugs.

3 DOSAGE FORMS AND STRENGTHS

For injection: 30 mg/vial or 140 mg/vial of polatuzumab vedotin-piiq as a white to grayish-white lyophilized powder in a single-dose vial for reconstitution and further dilution.

4 CONTRAINDICATIONS

None.

5 WARNINGS AND PRECAUTIONS

5.1 Peripheral Neuropathy

POLIVY can cause peripheral neuropathy, including severe cases. Peripheral neuropathy occurs as early as the first cycle of treatment and is a cumulative effect [see Adverse Reactions (6.1)]. POLIVY may exacerbate pre-existing peripheral neuropathy.

In POLARIX, of 435 patients treated with POLIVY plus R-CHP, 53% reported new or worsening peripheral neuropathy, with a median time to onset of 2.3 months. Peripheral neuropathy was Grade 1 in 39% of patients, Grade 2 in 12%, and Grade 3 in 1.6%. Peripheral neuropathy resulted in dose reduction in 4% of treated patients and treatment discontinuation in 0.7%. Among patients with peripheral neuropathy after POLIVY, 58% reported resolution after a median of 4 months.

In Study GO29365, of 173 patients treated with POLIVY, 40% reported new or worsening peripheral neuropathy, with a median time to onset of 2.1 months. Peripheral neuropathy was Grade 1 in 26% of patients, Grade 2 in 12%, and Grade 3 in 2.3%. Peripheral neuropathy resulted in POLIVY dose reduction in 2.9% of treated patients, dose delay in 1.2%, and permanent discontinuation in 2.9%. Sixty-five percent of patients reported improvement or resolution of peripheral neuropathy after a median of 1 month, and 48% reported complete resolution.

The peripheral neuropathy is predominantly sensory; however, motor and sensorimotor peripheral neuropathy also occur. Monitor for symptoms of peripheral neuropathy such as hypoesthesia, hyperesthesia, paresthesia, dysesthesia, neuropathic pain, burning sensation, weakness, or gait disturbance. Patients experiencing new or worsening peripheral neuropathy may require a delay, dose reduction, or discontinuation of POLIVY [see Dosage and Administration (2.2)].

5.2 Infusion-Related Reactions

POLIVY can cause infusion-related reactions, including severe cases. Delayed infusion-related reactions as late as 24 hours after receiving POLIVY have occurred.

With premedication, 13% of patients (58/435) in POLARIX reported infusion-related reactions after the administration of POLIVY plus R-CHP. The reactions were Grade 1 in 4.4% of patients, Grade 2 in 8%, and Grade 3 in 1.1%.

With premedication, 7% of patients (12/173) in Study GO29365 reported infusion-related reactions after the administration of POLIVY. The reactions were Grade 1 in 4.6% of patients, Grade 2 in 1.7%, and Grade 3 in 0.6%.

Symptoms occurring in ≥1% of patients included chills, dyspnea, pyrexia, pruritus, rash, and chest discomfort. Administer an antihistamine and antipyretic prior to the administration of POLIVY, and monitor patients closely throughout the infusion. If an infusion-related reaction occurs, interrupt the infusion and institute appropriate medical management [see Dosage and Administration (2.2)].

5.3 Myelosuppression

Treatment with POLIVY can cause serious or severe myelosuppression, including neutropenia, thrombocytopenia, and anemia.

In POLARIX, 90% of patients treated with POLIVY plus R-CHP had primary prophylaxis with G-CSF. Grade 3–4 hematologic adverse reactions included lymphopenia (44%), neutropenia (39%), febrile neutropenia (15%), anemia (14%), and thrombocytopenia (8%) [see Adverse Reactions (6.1)].

In Study GO29365, in patients treated with POLIVY plus BR (n = 45), 42% received primary prophylaxis with G-CSF. Grade 3 or higher hematologic adverse reactions included neutropenia (42%), thrombocytopenia (40%), anemia (24%), lymphopenia (13%), and febrile neutropenia (11%) [see Adverse Reactions (6.1)]. Grade 4 hematologic adverse reactions included neutropenia (24%), thrombocytopenia (16%), lymphopenia (9%), and febrile neutropenia (4.4%). Cytopenias were the most common reason for treatment discontinuation (18% of all patients).

Monitor complete blood counts throughout treatment. Cytopenias may require a delay, dose reduction, or discontinuation of POLIVY [see Dosage and Administration (2.2)]. Administer prophylactic G-CSF for neutropenia in patients receiving POLIVY plus R-CHP. Consider prophylactic G-CSF administration in patients receiving POLIVY plus bendamustine and a rituximab product.

5.4 Serious and Opportunistic Infections

Fatal and/or serious infections, including opportunistic infections such as sepsis, pneumonia (including Pneumocystis jiroveci and other fungal pneumonia), herpesvirus infection, and cytomegalovirus infection have occurred in patients treated with POLIVY [see Adverse Reactions (6.1)].

In POLARIX, Grade 3–4 infections occurred in 14% (61/435) of patients treated with POLIVY plus R-CHP and infection-related deaths were reported in 1.1% of patients.

In Study GO29365, Grade 3 or higher infections occurred in 32% (55/173) of patients treated with POLIVYand infection-related deaths were reported in 2.9% of patients within 90 days of last treatment.

Closely monitor patients during treatment for signs of infection. Administer prophylaxis for Pneumocystis jiroveci pneumonia and herpesvirus. Administer prophylactic G-CSF for neutropenia as recommended [see Dosage and Administration (2.3)].

5.5 Progressive Multifocal Leukoencephalopathy (PML)

PML has been reported after treatment with POLIVY plus bendamustine and obinutuzumab in study GO29365 (0.6%, 1/173). Monitor for new or worsening neurological, cognitive, or behavioral changes. Hold POLIVY and any concomitant chemotherapy if PML is suspected, and permanently discontinue if the diagnosis is confirmed.

5.6 Tumor Lysis Syndrome

POLIVY may cause tumor lysis syndrome. Patients with high tumor burden and rapidly proliferative tumor may be at increased risk of tumor lysis syndrome. Monitor closely and take appropriate measures, including tumor lysis syndrome prophylaxis.

5.7 Hepatotoxicity

Serious cases of hepatotoxicity that were consistent with hepatocellular injury, including elevations of transaminases and/or bilirubin, have occurred in patients treated with POLIVY.

In recipients of POLIVY plus R-CHP, Grade 3–4 elevation of ALT and AST developed in 1.4% and 0.7% of patients, respectively.

In Study GO29365, Grade 3 and Grade 4 transaminase elevations each developed in 1.9% of patients.

Preexisting liver disease, elevated baseline liver enzymes, and concomitant medications may increase the risk of hepatotoxicity. Monitor liver enzymes and bilirubin level.

5.8 Embryo-Fetal Toxicity

Based on the mechanism of action and findings from animal studies, POLIVY can cause fetal harm when administered to a pregnant woman. The small molecule component of POLIVY, MMAE, administered to rats caused adverse developmental outcomes, including embryo-fetal mortality and structural abnormalities, at exposures below those occurring clinically at the recommended dose.

Advise pregnant women of the potential risk to a fetus. Advise females of reproductive potential to use effective contraception during treatment with POLIVY and for 3 months after the last dose. Advise male patients with female partners of reproductive potential to use effective contraception during treatment with POLIVY and for 5 months after the last dose [see Use in Specific Populations (8.1, 8.3), Clinical Pharmacology (12.1)].

6 ADVERSE REACTIONS

The following clinically significant adverse reactions are discussed in greater detail in other sections of the label:

- Peripheral Neuropathy [see Warnings and Precautions (5.1)]
- Infusion-Related Reactions [see Warnings and Precautions (5.2)]
- Myelosuppression [see Warnings and Precautions (5.3)]
- Serious and Opportunistic Infections [see Warnings and Precautions (5.4)]
- Progressive Multifocal Leukoencephalopathy [see Warnings and Precautions (5.5)]
- Tumor Lysis Syndrome [see Warnings and Precautions (5.6)]
- Hepatotoxicity [see Warnings and Precautions (5.7)]

6.1 Clinical Trials Experience

Because clinical trials are conducted under widely varying conditions, adverse reaction rates observed in the clinical trials of a drug cannot be directly compared with rates in the clinical trials of another drug and may not reflect the rates observed in practice.

The safety data described below reflect exposure to POLIVY 1.8 mg/kg in 480 patients with large B-cell lymphoma (LBCL), including those with previously untreated LBCL (POLARIX) and relapsed or refractory DLBCL (GO29365).

Previously Untreated DLBCL, NOS or HGBL

GO39942 (POLARIX)

The safety of POLIVY in combination with R-CHP chemoimmunotherapy was evaluated in POLARIX, a randomized double-blind, placebo-controlled, multicenter study of 873 patients with previously untreated large B-cell lymphoma, 435 of whom received POLIVY plus R-CHP [see Clinical Studies (14.1)].

Patients were randomized 1:1 to receive POLIVY plus R-CHP or to receive R-CHOP for six 21-day cycles followed by two additional cycles of rituximab alone in both arms. Granulocyte colony-stimulating factor (G-CSF) primary prophylaxis was required and administered to 90% of patients in the POLIVY plus R-CHP arm and 93% of patients in the R-CHOP arm. Following premedication with an antihistamine and antipyretic, POLIVY was administered intravenously at 1.8 mg/kg on Day 1 of Cycles 1–6. R-CHP was administered starting on Day 1 of Cycles 1–6. Rituximab monotherapy was administered on Day 1 of Cycles 7–8 [see Clinical Studies (14.1)].

The trial required an absolute neutrophil count ≥1,000/µL, platelet count ≥75,000/µL, creatinine clearance (CLcr) ≥40 mL/min, hepatic transaminases ≤2.5 times the upper limit of normal (ULN), and bilirubin <1.5 times ULN, unless abnormalities were from the underlying disease. The trial excluded patients having age >80, ECOG performance status above 2, known central nervous system (CNS) lymphoma, and Grade 2 or higher peripheral neuropathy.

The median age was 65 years overall (range: 19 to 80 years); 54% of patients were male; 53% were White, 19% were Asian, 2%, Black or African American, and 5% were Hispanic or Latino.

In the POLIVY plus R-CHP group, 92% of patients received 6 cycles of POLIVY, and 94% completed 6 cycles of combination therapy.

Serious adverse reactions occurred in 34% of patients who received POLIVY plus R-CHP, including febrile neutropenia and pneumonia in ≥5% of recipients. Fatal adverse reactions occurred in 3% of recipients of POLIVY plus R-CHP within 90 days of last treatment, primarily from infection including pneumonia (0.9%) and sepsis (0.2%).

Adverse reactions led to dose reduction of POLIVY in 6% of patients, mainly from peripheral neuropathy. Adverse reactions lead to dose interruption of POLIVY in 18% of patients, most commonly from pneumonia and neutropenia, and permanent discontinuation of POLIVY in 4.4% of patients.

Table 6 summarizes adverse reactions in POLARIX. In recipients of POLIVY plus R-CHP, adverse reactions in ≥20% of patients, excluding laboratory abnormalities, were peripheral neuropathy, nausea, fatigue, diarrhea, constipation, alopecia, and mucositis. New or worsening Grade 3 to 4 laboratory abnormalities in ≥10% of patients were lymphopenia, neutropenia, hyperuricemia, and anemia.

Table 6 Select Adverse Reactions Occurring in ≥10% of Patients Treated with POLIVY Plus R-CHP in POLARIX
Adverse Reactions by Body System | POLIVY + R-CHP n = 435 |  | R-CHOP n = 438
Adverse Reactions by Body System | All Grades, % | Grade 3–4, % | All Grades, % | Grade 3–4, %
Blood and Lymphatic System Disorders [Laboratory values are based on integrated analysis of laboratory and adverse reaction data. Reported investigations exclude electrolytes.]
Lymphopenia | 80 | 44 | 77 | 44
Anemia | 68 | 14 | 67 | 11
Neutropenia | 60 | 39 | 60 | 42
Thrombocytopenia | 32 | 8 | 33 | 6
Febrile neutropenia [Febrile neutropenia includes febrile neutropenia, febrile bone marrow aplasia, and neutropenic sepsis.] | 15 | 15 | 9 | 9
Investigations
Creatinine increased | 66 | 0.7 | 64 | 0.9
Aspartate aminotransferase increased | 26 | 0.7 | 23 | 1.1
Alanine aminotransferase increased | 25 | 1.4 | 27 | 0.5
Alkaline phosphatase increased | 23 | 0 | 22 | 0.5
Uric acid increased | 19 | 18 | 17 | 16
Weight decreased | 13 | 0.9 | 12 | 0.2
Nervous System Disorders
Peripheral neuropathy [At last assessment, peripheral neuropathy was unresolved in 42% in the POLIVY + R-CHP arm and in 33% in the R-CHOP arm.] , [Peripheral neuropathy includes all terms containing "neuropathy", neuralgia, dysesthesia, paresthesia, hypoesthesia, peroneal nerve palsy, hypotonia, hyporeflexia, neuromyopathy, and hyperesthesia.] | 53 | 1.6 | 54 | 1.1
Altered taste | 14 | 0 | 16 | 0
Headache | 13 | 0.2 | 14 | 0.9
Gastrointestinal Disorders
Nausea | 42 | 1.1 | 37 | 0.5
Diarrhea | 31 | 3.9 | 20 | 1.8
Constipation | 29 | 1.1 | 29 | 0.2
Mucositis [Mucositis includes stomatitis, oropharyngeal pain, mucosal inflammation, mouth ulceration, oral pain, oropharyngeal discomfort, aphthous ulcer, odynophagia, oral discomfort, tongue blistering, and tongue ulceration.] | 22 | 1.4 | 19 | 0.5
Abdominal pain [Abdominal pain includes abdominal pain, abdominal discomfort, gastrointestinal pain, epigastric discomfort, and related terms.] | 16 | 1.1 | 14 | 1.6
Vomiting | 15 | 1.1 | 14 | 0.7
General Disorders
Fatigue | 37 | 2.5 | 38 | 3.0
Pyrexia | 16 | 1.4 | 13 | 0
Edema [Edema includes edema, face edema, swelling face, edema peripheral, fluid overload, fluid retention, pulmonary edema, peripheral swelling, and swelling.] | 14 | 0.5 | 11 | 0.2
Infusion-related reaction [Infusion related reaction is reflective of the combination regimen due to same-day administration.] | 13 | 1.1 | 16 | 1.6
Skin and Subcutaneous Tissue Disorders
Alopecia | 24 | 0 | 24 | 0.2
Rash [Rash includes rash, dermatitis, and related terms.] | 13 | 0.7 | 11 | 0
Musculoskeletal Disorders
Musculoskeletal pain [Musculoskeletal pain includes musculoskeletal pain, back pain, musculoskeletal chest pain, neck pain, myalgia, and bone pain.] | 19 | 0.5 | 21 | 1.8
Infections
Upper respiratory tract infection [Upper respiratory tract infection incudes sinusitis, laryngitis, pharyngitis, nasopharyngitis, rhinitis, and specific infections.] | 17 | 0.5 | 16 | 0.5
Metabolism and Nutrition Disorders
Decreased appetite | 17 | 1.1 | 14 | 0.7
Respiratory Disorders
Cough | 15 | 0 | 14 | 0
Dyspnea | 13 | 0.9 | 10 | 0.9
The table includes a combination of grouped and ungrouped terms. Events were graded using NCI CTCAE version 4.0.

Other clinically relevant adverse reactions in <10% of recipients of POLIVY plus R-CHP included:

- Infections: pneumonia, herpesvirus infection, sepsis, cytomegalovirus infection
- Metabolic disorders: tumor lysis syndrome
- Renal disorders: renal insufficiency
- Respiratory disorders: pneumonitis

Relapsed or Refractory DLBCL, NOS

GO29365

The data described in this section reflect exposure to POLIVY in Study GO29365, a multicenter clinical trial for adult patients with relapsed or refractory B-cell lymphomas [see Clinical Studies (14.2)]. In patients with relapsed or refractory DLBCL, the trial included a single-arm safety evaluation of POLIVY in combination with bendamustine and a rituximab product (BR) (n = 6), followed by an open-label randomization to POLIVY in combination with BR versus BR alone (n = 39 treated per arm).

Following premedication with an antihistamine and antipyretic, POLIVY 1.8 mg/kg was administered by intravenous infusion on Day 2 of Cycle 1 and on Day 1 of Cycles 2–6, with a cycle length of 21 days. Bendamustine 90 mg/m^2 daily was administered intravenously on Days 2 and 3 of Cycle 1 and on Days 1 and 2 of Cycles 2–6. A rituximab product dosed at 375 mg/m^2 was administered intravenously on Day 1 of each cycle. Granulocyte colony-stimulating factor primary prophylaxis was optional and administered to 42% of recipients of POLIVY plus BR.

In POLIVY-treated patients (n = 45), the median age was 67 years (range 33 – 86) with 58% being ≥age 65, 69% were male, 69% were White, and 87% had an Eastern Cooperative Oncology Group (ECOG) performance status of 0 or 1. The trial required an absolute neutrophil count ≥1500/µL, platelet count ≥75/µL, creatinine clearance (CLcr) ≥40 mL/min, hepatic transaminases ≤2.5 times ULN, and bilirubin <1.5 times ULN, unless abnormalities were from the underlying disease. Patients with Grade 2 or higher peripheral neuropathy or prior allogeneic hematopoietic stem cell transplantation (HSCT) were excluded.

Patients treated with POLIVY plus BR received a median of 5 cycles, with 49% receiving 6 cycles. Patients treated with BR alone received a median of 3 cycles, with 23% receiving 6 cycles.

Fatal adverse reactions occurred in 7% of recipients of POLIVY plus BR within 90 days of last treatment. Serious adverse reactions occurred in 64%, most often from infection. Serious adverse reactions in ≥5% of recipients of POLIVY plus BR included pneumonia (16%), febrile neutropenia (11%), pyrexia (9%), and sepsis (7%).

In recipients of POLIVY plus BR, adverse reactions led to dose reduction in 18%, dose interruption in 51%, and permanent discontinuation of all treatment in 31%. The most common adverse reactions leading to treatment discontinuation were thrombocytopenia and/or neutropenia.

Table 7 summarizes commonly reported adverse reactions. In recipients of POLIVY plus BR, adverse reactions in ≥20% of patients included neutropenia, thrombocytopenia, anemia, peripheral neuropathy, fatigue, diarrhea, pyrexia, decreased appetite, and pneumonia.

Table 7 Adverse Reactions Occurring in >10% of Patients with Relapsed or Refractory DLBCL and ≥5% More in the POLIVY Plus Bendamustine and Rituximab Product Group in Study GO29365
Adverse Reactions by Body System | POLIVY + BR n = 45 |  | BR n = 39
Adverse Reactions by Body System | All Grades, % | Grade 3 or Higher, % | All Grades, % | Grade 3 or Higher, %
Blood and Lymphatic System Disorders
Neutropenia | 49 | 42 | 44 | 36
Thrombocytopenia | 49 | 40 | 33 | 26
Anemia | 47 | 24 | 28 | 18
Lymphopenia | 13 | 13 | 8 | 8
Nervous System Disorders
Peripheral neuropathy | 40 | 0 | 8 | 0
Dizziness | 13 | 0 | 8 | 0
Gastrointestinal Disorders
Diarrhea | 38 | 4.4 | 28 | 5
Vomiting | 18 | 2.2 | 13 | 0
General Disorders
Infusion-related reaction | 18 | 2.2 | 8 | 0
Pyrexia | 33 | 2.2 | 23 | 0
Decreased appetite | 27 | 2.2 | 21 | 0
Infections
Pneumonia | 22 | 16 [Includes 2 fatalities.] | 15 | 2.6 [Includes 1 fatality.]
Upper respiratory tract infection | 13 | 0 | 8 | 0
Investigations
Weight decreased | 16 | 2.2 | 8 | 2.6
Metabolism and Nutrition Disorders
Hypokalemia | 16 | 9 | 10 | 2.6
Hypoalbuminemia | 13 | 2.2 | 8 | 0
Hypocalcemia | 11 | 2.2 | 5 | 0
The table includes a combination of grouped and ungrouped terms. Events were graded using NCI CTCAE version 4.

Other clinically relevant adverse reactions (<10% or with a <5% difference) in recipients of POLIVY plus BR included:

- Blood and lymphatic system disorders: pancytopenia (7%)
- Musculoskeletal disorders: arthralgia (7%)
- Investigations: hypophosphatemia (9%), transaminase elevation (7%), lipase increased (7%)
- Respiratory disorders: pneumonitis (4.4%)

Selected treatment-emergent laboratory abnormalities are summarized in Table 8. In recipients of POLIVY plus BR, >20% of patients developed Grade 3 or 4 neutropenia, leukopenia, or thrombocytopenia, and >10% developed Grade 4 neutropenia (13%) or Grade 4 thrombocytopenia (11%).

Table 8 Select Laboratory Abnormalities Worsening from Baseline in Patients with Relapsed or Refractory DLBCL and ≥5% More in the POLIVY Plus Bendamustine and Rituximab Product Group
Laboratory Parameter [Includes laboratory abnormalities that are new or worsening in grade or with worsening from baseline unknown.] | POLIVY + BR n = 45 |  | BR n = 39
Laboratory Parameter [Includes laboratory abnormalities that are new or worsening in grade or with worsening from baseline unknown.] | All Grades, (%) | Grade 3–4, (%) | All Grades, (%) | Grade 3–4, (%)
Hematologic
Lymphocyte count decreased | 87 | 87 | 90 | 82
Neutrophil count decreased | 78 | 61 | 56 | 33
Hemoglobin decreased | 78 | 18 | 62 | 10
Platelet count decreased | 76 | 31 | 64 | 26
Chemistry
Creatinine increased | 87 | 4.4 | 77 | 5
Calcium decreased | 44 | 9 | 26 | 0
SGPT/ALT increased | 38 | 0 | 8 | 2.6
SGOT/AST increased | 36 | 0 | 26 | 2.6
Lipase increased | 36 | 9 | 13 | 5
Phosphorus decreased | 33 | 7 | 28 | 8
Amylase increased | 24 | 0 | 18 | 2.6
Potassium decreased | 24 | 11 | 28 | 5

Safety was also evaluated in 173 adult patients with relapsed or refractory lymphoma who received POLIVY, bendamustine, and either a rituximab product or obinutuzumab in Study GO29365, including the 45 patients with DLBCL described above. In the expanded safety population, the median age was 66 years (range 27 – 86), 57% were male, 91% had an ECOG performance status of 0-1, and 32% had a history of peripheral neuropathy at baseline.

Fatal adverse reactions occurred in 4.6% of recipients of POLIVY within 90 days of last treatment, with infection as a leading cause. Serious adverse reactions occurred in 60%, most often from infection.

Table 9 summarizes the most common adverse reactions in the expanded safety population. The overall safety profile was similar to that described above. Adverse reactions in ≥20% of patients were diarrhea, neutropenia, peripheral neuropathy, fatigue, thrombocytopenia, pyrexia, decreased appetite, anemia, and vomiting. Infection-related adverse reactions in >10% of patients included upper respiratory tract infection, febrile neutropenia, pneumonia, and herpesvirus infection.

Table 9 Most Common Adverse Reactions (≥20% Any Grade or ≥5% Grade 3 or Higher) in Recipients of POLIVY and Chemoimmunotherapy for Relapsed or Refractory Lymphoma
Adverse Reaction by Body System | POLIVY + Bendamustine + Rituximab Product or Obinutuzumab n = 173
Adverse Reaction by Body System | All Grades, % | Grade 3 or Higher, %
Blood and Lymphatic System Disorders
Neutropenia | 44 | 39
Thrombocytopenia | 31 | 23
Anemia | 28 | 14
Febrile neutropenia [Primary prophylaxis with granulocyte colony-stimulating factor was given to 46% of all patients.] | 13 | 13
Leukopenia | 13 | 8
Lymphopenia | 12 | 12
Nervous System Disorders
Peripheral neuropathy | 40 | 2.3
Gastrointestinal Disorders
Diarrhea | 45 | 8
Vomiting | 27 | 2.9
General Disorders
Fatigue | 40 | 5
Pyrexia | 30 | 2.9
Decreased appetite | 29 | 1.7
Infections
Pneumonia | 13 | 10 [Includes 5 fatalities.]
Sepsis | 6 | 6 [Includes 4 fatalities.]
Metabolism and Nutrition Disorders
Hypokalemia | 18 | 6
The table includes a combination of grouped and ungrouped terms.

Other clinically relevant adverse reactions (<20% any grade) included:

- General disorders: infusion-related reaction (7%)
- Infection: upper respiratory tract infection (16%), lower respiratory tract infection (10%), herpesvirus infection (12%), cytomegalovirus infection (1.2%)
- Respiratory: dyspnea (19%), pneumonitis (1.7%)
- Nervous system disorders: dizziness (10%)
- Investigations: weight decrease (10%), transaminase elevation (8%), lipase increase (3.5%)
- Musculoskeletal disorders: arthralgia (7%)
- Eye disorders: blurred vision (1.2%)

7 DRUG INTERACTIONS

7.1 Effects of Other Drugs on POLIVY

Strong CYP3A Inhibitors

Concomitant use with a strong CYP3A4 inhibitor may increase unconjugated MMAE AUC [see Clinical Pharmacology (12.3)], which may increase POLIVY toxicities. Monitor patients for signs of toxicity.

Strong CYP3A Inducers

Concomitant use with a strong CYP3A4 inducer may decrease unconjugated MMAE AUC [see Clinical Pharmacology (12.3)].

8 USE IN SPECIFIC POPULATIONS

8.1 Pregnancy

Risk Summary

Based on findings from animal studies and its mechanism of action [see Clinical Pharmacology (12.1)], POLIVY can cause fetal harm. There are no available data in pregnant women to inform the drug-associated risk. In animal reproduction studies, administration of the small molecule component of POLIVY, MMAE, to pregnant rats during organogenesis at exposures below the clinical exposure at the recommended dose of 1.8 mg/kg POLIVY every 21 days resulted in embryo-fetal mortality and structural abnormalities (see Data). Advise a pregnant woman of the potential risks to a fetus.

The estimated background risk of major birth defects and miscarriage for the indicated population is unknown. All pregnancies have a background risk of birth defect, loss, or other adverse outcomes. In the U.S. general population, the estimated background risk of major birth defects and miscarriage in clinically recognized pregnancies is 2–4% and 15–20%, respectively.

Data

Animal Data

No embryo-fetal development studies in animals have been performed with polatuzumab vedotin-piiq. In an embryo-fetal developmental study in pregnant rats, administration of two intravenous doses of MMAE, the small molecule component of POLIVY, on gestational days 6 and 13 caused embryo-fetal mortality and structural abnormalities, including protruding tongue, malrotated limbs, gastroschisis, and agnathia compared to controls at a dose of 0.2 mg/kg (approximately 0.5-fold the human area under the curve [AUC] at the recommended dose).

8.2 Lactation

Risk Summary

There is no information regarding the presence of polatuzumab vedotin-piiq in human milk, the effects on the breastfed child, or milk production. Because of the potential for serious adverse reactions in breastfed children, advise women not to breastfeed during treatment with POLIVY and for 2 months after the last dose.

8.3 Females and Males of Reproductive Potential

POLIVY can cause embryo-fetal harm when administered to pregnant women [see Use in Specific Populations (8.1)].

Pregnancy Testing

Verify pregnancy status in females of reproductive potential prior to initiating POLIVY [see Use in Specific Populations (8.1)].

Contraception

Females

Advise females of reproductive potential to use effective contraception during treatment with POLIVY and for 3 months after the last dose [see Nonclinical Toxicology (13.1)].

Males

Based on genotoxicity findings, advise males with female partners of reproductive potential to use effective contraception during treatment with POLIVY and for 5 months after the final dose [see Nonclinical Toxicity (13.1)].

Infertility

Females

Based on findings in animal studies with MMAE-containing antibody-drug conjugates (ADCs), POLIVY may impair female fertility. The effect on fertility is reversible [see Nonclinical Toxicology (13.1)].

Males

Based on findings from animal studies, POLIVY may impair male fertility. The reversibility of this effect is unknown [see Nonclinical Toxicology (13.1)].

8.4 Pediatric Use

Safety and effectiveness of POLIVY have not been established in pediatric patients.

8.5 Geriatric Use

Among 435 patients treated with POLIVY plus R-CHP in POLARIX, 227 (52%) were ≥65 years of age. No overall differences in safety or efficacy were observed between patients aged ≥65 years and younger patients.

Among 173 patients treated with POLIVY plus BR in Study GO29365, 95 (55%) were ≥65 years of age. Patients aged ≥65 had a numerically higher incidence of serious adverse reactions (64%) than patients aged <65 (53%). This study did not include sufficient numbers of patients to determine whether efficacy differed in patients aged ≥65 and younger patients.

8.6 Hepatic Impairment

Avoid the administration of POLIVY in patients with moderate or severe hepatic impairment (total bilirubin greater than 1.5 × ULN and any AST). Patients with moderate or severe hepatic impairment are likely to have increased exposure to MMAE, which may increase the risk of adverse reactions. POLIVY has not been studied in patients with moderate or severe hepatic impairment [see Clinical Pharmacology (12.3) and Warnings and Precautions (5.7)].

No adjustment in the starting dose is required when administering POLIVY to patients with mild hepatic impairment (total bilirubin 1 to 1.5 × ULN or AST greater than ULN).

11 DESCRIPTION

Polatuzumab vedotin-piiq is a CD79b-directed antibody and microtubule inhibitor conjugate. It consists of three components: 1) the humanized immunoglobulin G1 (IgG1) monoclonal antibody specific for human CD79b; 2) the small molecule anti-mitotic agent MMAE; and 3) a protease-cleavable linker maleimidocaproyl-valine-citrulline-p-aminobenzyloxycarbonyl (mc-vc-PAB) that covalently attaches MMAE to the polatuzumab antibody.

Polatuzumab vedotin-piiq has an approximate molecular weight of 150 kDa. An average of 3.5 molecules of MMAE are attached to each antibody molecule. Polatuzumab vedotin-piiq is produced by chemical conjugation of the antibody and small molecule components. The antibody is produced by mammalian (Chinese hamster ovary) cells, and the small molecule components are produced by chemical synthesis.

POLIVY (polatuzumab vedotin-piiq) for injection is supplied as a sterile, white to grayish-white, preservative-free, lyophilized powder, which has a cake-like appearance, for intravenous infusion after reconstitution and dilution.

Each single-dose 30 mg POLIVY vial delivers 30 mg of polatuzumab vedotin-piiq, polysorbate-20 (1.8 mg), sodium hydroxide (0.82 mg), succinic acid (1.77 mg), and sucrose (62 mg). After reconstitution with 1.8 mL of Sterile Water for Injection, USP, the final concentration is 20 mg/mL with a pH of approximately 5.3.

Each single-dose 140 mg POLIVY vial delivers 140 mg of polatuzumab vedotin-piiq, polysorbate-20 (8.4 mg), sodium hydroxide (3.80 mg), succinic acid (8.27 mg), and sucrose (288 mg). After reconstitution with 7.2 mL of Sterile Water for Injection, USP, the final concentration is 20 mg/mL with a pH of approximately 5.3.

The POLIVY vial stoppers are not made with natural rubber latex.

12 CLINICAL PHARMACOLOGY

12.1 Mechanism of Action

Polatuzumab vedotin-piiq is a CD79b-directed antibody-drug conjugate with activity against dividing B cells. The small molecule, MMAE, is an anti-mitotic agent covalently attached to the antibody via a cleavable linker. The monoclonal antibody binds to CD79b, a B-cell specific surface protein, which is a component of the B-cell receptor. Upon binding CD79b, polatuzumab vedotin-piiq is internalized, and the linker is cleaved by lysosomal proteases to enable intracellular delivery of MMAE. MMAE binds to microtubules and kills dividing cells by inhibiting cell division and inducing apoptosis.

12.2 Pharmacodynamics

Over polatuzumab vedotin-piiq dosages of 0.1 to 2.4 mg/kg (0.06 to 1.33 times the approved recommended dosage), higher exposures (AUC and Cmax) of antibody-conjugated MMAE (acMMAE) and unconjugated MMAE were associated with higher incidence of some adverse reactions (including ≥Grade 3 thrombocytopenia and ≥Grade 3 anemia). Higher exposure (AUC and Cmax) of unconjugated MMAE was associated with higher incidence of ≥Grade 2 peripheral neuropathy. Lower acMMAE exposure (AUC) was associated with lower efficacy in patients with relapsed or refractory DLBCL.

Cardiac Electrophysiology

Polatuzumab vedotin-piiq did not prolong the mean QTc interval to any clinically relevant extent based on ECG data from two open-label studies in patients with previously treated B-cell malignancies at the recommended dosage.

12.3 Pharmacokinetics

The exposure parameters of acMMAE and unconjugated MMAE (the cytotoxic component of polatuzumab vedotin-piiq) are summarized in Table 10. The plasma exposure of acMMAE and unconjugated MMAE increased proportionally over a polatuzumab vedotin-piiq dose range from 0.1 to 2.4 mg/kg (0.06 to 1.33 times the approved recommended dosage). Cycle 3 acMMAE AUC were predicted to increase by approximately 30% over Cycle 1 AUC, and achieved more than 90% of the Cycle 6 AUC. Unconjugated MMAE plasma exposures were <3% of acMMAE exposures, and the AUC and Cmax were predicted to decrease after repeated every-3-week dosing.

Table 10 Cycle 1 Exposure of acMMAE and Unconjugated MMAE [After the first polatuzumab vedotin-piiq dose of 1.8 mg/kg.] , [Cycle 1 exposures are reported as Geometric Mean (Geometric Coefficient of Variation %).]
 | R/R DLBCL, NOS |  | Previously Untreated DLBCL, NOS or HGBL
 | acMMAE | Unconjugated MMAE | acMMAE | Unconjugated MMAE
Cmax (ng/mL) | 688 (15%) | 3.19 (57%) | 587 (15%) | 2.45 (46%)
AUC (day*ng/mL) | 2040 (35%) | 31.0 (56%) | 1690 (22%) | 20.8 (50%)
Cmax=maximum concentration; AUC=area under the concentration-time curve from time zero to day 21.

Distribution

The acMMAE central volume of distribution is 3.15 L. For humans, MMAE plasma protein binding is 71% to 77% and the blood-to-plasma ratio is 0.79 to 0.98, in vitro.

Elimination

At the end of Cycle 6, the median (min, max) acMMAE terminal half-life was 12.2 days (4.5 to 36.7 days) and the clearance was 0.9 L/day in patients with B-cell malignancies. The median (min, max) unconjugated MMAE terminal half-life was 3.74 days (1.58 to 10.1 days) days after the first polatuzumab vedotin-piiq dose.

Metabolism

Polatuzumab vedotin-piiq catabolism has not been studied in humans; however, it is expected to undergo catabolism to small peptides, amino acids, unconjugated MMAE, and unconjugated MMAE-related catabolites. MMAE is a substrate for CYP3A4.

Specific Populations

No clinically significant differences in the pharmacokinetics of acMMAE or unconjugated MMAE were observed based on age (19 to 89 years), sex (males versus females), race (White 69%, Asian 11%), or mild to moderate renal impairment (CLcr 30 to 89 mL/min).

The effect of severe renal impairment (CLcr 15 to 29 mL/min) or end-stage renal disease with or without dialysis on the pharmacokinetics of acMMAE or unconjugated MMAE is unknown.

Patients with Hepatic Impairment

Compared to patients with normal hepatic function, geometric mean MMAE exposure was 11% higher in patients with previously untreated DLBCL and mild hepatic impairment (total bilirubin 1 to 1.5 × ULN or any AST greater than ULN) and 40% higher in patients with relapsed or refractory DLBCL and mild hepatic impairment. The effect of mild hepatic impairment on MMAE exposure is not expected to have a clinically significant impact.

Mild hepatic impairment was not associated with a significant difference in acMMAE exposure. The effect of moderate to severe hepatic impairment (total bilirubin greater than 1.5 × ULN and any AST) or liver transplantation on the pharmacokinetics of acMMAE or unconjugated MMAE is unknown.

Drug Interaction Studies

No dedicated clinical drug-drug interaction studies with POLIVY in humans have been conducted.

Physiologically-Based Pharmacokinetic (PBPK) Modeling Predictions:

Strong CYP3A Inhibitor: Concomitant use of polatuzumab vedotin-piiq with ketoconazole (strong CYP3A inhibitor) is predicted to increase unconjugated MMAE AUC by 45%.

Strong CYP3A Inducer: Concomitant use of polatuzumab vedotin-piiq with rifampin (strong CYP3A inducer) is predicted to decrease unconjugated MMAE AUC by 63%.

Sensitive CYP3A Substrate: Concomitant use of polatuzumab vedotin-piiq is predicted not to affect exposure to midazolam (sensitive CYP3A substrate).

Population Pharmacokinetic (popPK) Modeling Predictions:

Bendamustine or Rituximab: No clinically significant differences in the pharmacokinetics of acMMAE or unconjugated MMAE are predicted when polatuzumab vedotin-piiq is used concomitantly with bendamustine or rituximab.

Rituximab, Cyclophosphamide, Doxorubicin, or Prednisone (R-CHP): No clinically significant differences in the pharmacokinetics of acMMAE or unconjugated MMAE are predicted when polatuzumab vedotin-piiq is used concomitantly with R-CHP.

In Vitro Studies Where Drug Interaction Potential Was Not Further Evaluated Clinically:

Cytochrome P450 (CYP) Enzymes: MMAE does not inhibit CYP1A2, CYP2B6, CYP2C8, CYP2C9, CYP2C19, or CYP2D6. MMAE does not induce major CYP enzymes.

Transporter Systems: MMAE does not inhibit P-gp. MMAE is a P-gp substrate.

12.6 Immunogenicity

The observed incidence of anti-drug antibodies is highly dependent on the sensitivity and specificity of the assay. Differences in assay methods preclude meaningful comparisons of the incidence of anti-drug antibodies in the studies described below with the incidence of anti-drug antibodies in other studies, including those of POLIVY or of other polatuzumab products.

In studies POLARIX and GO29365, 1.4% (6/427) and 6% (8/134) of patients tested positive for antibodies against polatuzumab vedotin-piiq, respectively, of which none were positive for neutralizing antibodies. Because of the low occurrence of anti-drug antibodies, the effect of these antibodies on the pharmacokinetics, pharmacodynamics, safety, and/or effectiveness of polatuzumab products is unknown.

13 NONCLINICAL TOXICOLOGY

13.1 Carcinogenesis, Mutagenesis, Impairment of Fertility

Carcinogenicity studies in animals have not been performed with polatuzumab vedotin-piiq or MMAE.

MMAE was positive for genotoxicity in the in vivo rat bone marrow micronucleus study through an aneugenic mechanism. MMAE was not mutagenic in the bacterial reverse mutation (Ames) assay or the L5178Y mouse lymphoma forward mutation assay.

Fertility studies in animals have not been performed with polatuzumab vedotin-piiq or MMAE. However, results of repeat-dose toxicity indicate the potential for polatuzumab vedotin-piiq to impair female and male fertility. In the 4-week repeat-dose toxicity study in rats with weekly dosing of 2, 6, and 10 mg/kg, dose-dependent testicular seminiferous tubule degeneration with abnormal lumen contents in the epididymis was observed. Findings in the testes and epididymis did not reverse and correlated with decreased testes weight and gross findings of small and/or soft testes at recovery necropsy in males given doses ≥2 mg/kg (below the exposure at the recommended dose based on unconjugated MMAE AUC).

MMAE-containing ADCs have been associated with adverse ovarian effects when administered to sexually immature animals. Adverse effects included decrease in, or absence of, secondary and tertiary ovarian follicles after weekly administration to cynomolgus monkeys in studies of 4-week duration. These effects showed a trend towards recovery 6 weeks after the end of dosing; no changes were observed in primordial follicles.

14 CLINICAL STUDIES

14.1 Previously Untreated DLBCL, NOS or HGBL

GO39942 (POLARIX)

The efficacy of POLIVY was evaluated in POLARIX (NCT03274492), a randomized double-blind, placebo-controlled, multicenter trial in patients with previously untreated large B-cell lymphoma. Eligible patients were aged 18–80 and had an International Prognostic Index (IPI) score of 2–5 and ECOG performance status of 0–2. The study excluded patients with transformed lymphoma, primary mediastinal large B-cell lymphoma, known CNS lymphoma, or Grade 2 or higher peripheral neuropathy.

Patients were randomized in a 1:1 ratio to receive POLIVY plus R-CHP or to receive R-CHOP for six 21-day cycles followed by two additional cycles of rituximab alone in both arms. Randomization was stratified by IPI score (2 vs 3–5), presence or absence of bulky disease (lesion ≥7.5 cm), and geographical region. Dosing in each treatment arm was as follows:

- POLIVY + R-CHP arm: POLIVY 1.8 mg/kg intravenously, rituximab 375 mg/m^2 intravenously, cyclophosphamide 750 mg/m^2 intravenously, and doxorubicin 50 mg/m^2 intravenously on Day 1 and prednisone 100 mg orally once daily on Days 1–5 for 6 cycles. Rituximab 375 mg/m^2 was administered intravenously on Day 1 of cycles 7 and 8.
- R-CHOP arm: rituximab 375 mg/m^2 intravenously, cyclophosphamide 750 mg/m^2 intravenously, doxorubicin 50 mg/m^2 intravenously, and vincristine 1.4 mg/m^2 intravenously on Day 1 and prednisone 100 mg orally once daily on Days 1–5 for 6 cycles. Rituximab 375 mg/m^2 was administered intravenously on Day 1 of cycles 7 and 8.

Prophylaxis with granulocyte-colony stimulating factor (G-CSF) was mandated for both arms. Dosing in both treatment arms was preceded by premedication.

Of the 879 patients randomized (440 to POLIVY plus R-CHP, 439 to R-CHOP), the median age was 65 years (range 19 to 80 years), 54% were male, 54% were White, 19% were Asian, 1.8% were Black or African American, and 6% were Hispanic or Latino. In total, 38% had an IPI score of 2, 62% had an IPI score of 3–5, 89% had Stage 3 or 4 disease, and 44% had bulky disease. The majority of patients had DLBCL, NOS (84%; n = 740), 11% (n = 93) had HGBL with MYC and BCL2 and/or BCL6 rearrangements or HGBL, NOS, and 5% had other large B-cell lymphomas.

Efficacy was based on investigator-assessed progression-free survival (PFS). Other efficacy measures included modified event-free survival. Efficacy results are summarized in Table 11 and in Figure 1.

Table 11 Summary of Efficacy in POLARIX by Intention-to-Treat Analysis
Outcomes | POLIVY + R-CHP n = 440 | R-CHOP n = 439
Progression-Free Survival per Investigator [Estimated median follow-up for PFS was 24.7 months in both arms combined.]
Number (%) of patients with event | 107 (24) | 134 (31)
Progression | 88 | 114
Death | 19 | 20
HR (95% CI) | 0.73 (0.57, 0.95)
p-value [Stratified log-rank test, with a two-sided significance boundary of 0.05. The hierarchical testing order was PFS, modified EFS, then CR rate and overall survival.] | 0.0177
Modified Event-Free Survival per Investigator [Modified EFS was defined as time from randomization to the earliest occurrence of disease progression or relapse, death, an efficacy finding that led to non-protocol specified lymphoma treatment, or biopsy positive for residual disease.]
Number (%) of patients with event | 112 (26) | 138 (31)
HR (95% CI) | 0.75 (0.58, 0.96)
p-value | 0.0244
Objective Response at End of Treatment [By blinded independent central review, per 2014 Lugano response criteria.]
Objective response rate, % (95% CI) | 86 (82, 89) | 84 (80, 87)
CR rate, % | 78 (74, 82) | 74 (70, 78)
Difference in CR rate, % (95% CI) | 3.9 (–1.9, 9.7)
p-value [Cochran-Mantel-Haenszel chi-squared test, with a two-sided significance boundary of 0.01.] | 0.1557
CI=confidence interval; CR=complete response; EFS=event-free survival; HR=hazard ratio; PFS=progression-free survival.

Figure 1 Kaplan-Meier Curve of Investigator-Assessed Progression-Free Survival in POLARIX by Intention-to-Treat Analysis

In a prespecified descriptive analysis of the largest lymphoma subgroup, DLBCL, NOS, the PFS HR was 0.75 (95% CI: 0.57, 0.99). In patients with HGBL, the PFS HR was 0.48 (95% CI: 0.21, 1.08). There were insufficient data to evaluate efficacy in other large B-cell lymphomas.

With an estimated median follow-up of 3.3 years, the prespecified final analysis of overall survival (OS) showed no statistically significant difference, with a HR of 0.94 (95% CI: 0.67, 1.33). In a descriptive analysis, the OS HR in patients with DLBCL, NOS was 1.02 (95% CI: 0.70, 1.49). The OS HR in patients with HGBL was 0.42 (95% CI: 0.15, 1.19).

14.2 Relapsed or Refractory DLBCL, NOS

GO29365

The efficacy of POLIVY was evaluated in Study GO29365 (NCT02257567), an open-label, multicenter clinical trial that included a cohort of 80 patients with relapsed or refractory DLBCL after at least one prior regimen. Patients were randomized 1:1 to receive either POLIVY in combination with bendamustine and a rituximab product (BR) or BR alone for six 21-day cycles. Randomization was stratified by duration of response (DOR) to last therapy. Eligible patients were not candidates for autologous HSCT at study entry. The study excluded patients with Grade 2 or higher peripheral neuropathy, prior allogeneic HSCT, active central nervous system lymphoma, or transformed lymphoma.

Following premedication with an antihistamine and antipyretic, POLIVY was given by intravenous infusion at 1.8 mg/kg on Day 2 of Cycle 1 and on Day 1 of Cycles 2–6. Bendamustine was administered at 90 mg/m^2 intravenously daily on Days 2 and 3 of Cycle 1 and on Days 1 and 2 of Cycles 2–6. A rituximab product was administered at a dose of 375 mg/m^2 intravenously on Day 1 of Cycles 1–6. The cycle length was 21 days.

Of the 80 patients randomized to receive POLIVY plus BR (n = 40) or BR alone (n = 40), the median age was 69 years (range: 30–86 years), 66% were male, and 71% were White. Most patients (98%) had DLBCL not otherwise specified. The primary reasons patients were not candidates for HSCT included age (40%), insufficient response to salvage therapy (26%), and prior transplant failure (20%). The median number of prior therapies was 2 (range: 1–7), with 29% receiving one prior therapy, 25% receiving 2 prior therapies, and 46% receiving 3 or more prior therapies. Eighty percent of patients had refractory disease to last therapy.

In the POLIVY plus BR arm, patients received a median of 5 cycles, with 49% receiving 6 cycles. In the BR arm, patients received a median of 3 cycles, with 23% receiving 6 cycles.

Efficacy was based on complete response (CR) rate at the end of treatment and DOR, as determined by an independent review committee (IRC). Other efficacy measures included IRC-assessed best overall response.

Response rates are summarized in Table 12.

Table 12 Response Rates in Patients with Relapsed or Refractory DLBCL
Response per IRC, n (%) [PET-CT based response per modified Lugano 2014 criteria. Bone marrow confirmation of PET-CT CR was required. PET-CT PR required meeting both PET criteria and CT criteria for PR.] | POLIVY + BR n = 40 | BR n = 40
Objective Response at End of Treatment [End of treatment was defined as 6–8 weeks after Day 1 of Cycle 6 or last study treatment.] (95% CI) | 18 (45) (29, 62) | 7 (18) (7, 33)
CR (95% CI) | 16 (40) (25, 57) | 7 (18) (7, 33)
Difference in CR rates, % (95% CI) [Miettinen-Nurminen method.] | 22 (3, 41)
Best Overall Response of CR or PR [PET-CT results were prioritized over CT results.] (95% CI) | 25 (63) (46, 77) | 10 (25) (13, 41)
Best Response of CR (95% CI) | 20 (50) (34, 66) | 9 (23) (11, 38)
CR=complete response; PR=partial remission.

In the POLIVY plus BR arm, of the 25 patients who achieved a partial or complete response, 16 (64%) had a DOR of at least 6 months, and 12 (48%) had a DOR of at least 12 months. In the BR arm, of the 10 patients who achieved a partial or complete response, 3 (30%) had a DOR lasting at least 6 months, and 2 (20%) had a DOR lasting at least 12 months.

15 REFERENCES

1. "OSHA Hazardous Drugs." OSHA. http://www.osha.gov/SLTC/hazardousdrugs/index.html

16 HOW SUPPLIED/STORAGE AND HANDLING

How Supplied

POLIVY (polatuzumab vedotin-piiq) for injection is a preservative-free, white to grayish-white lyophilized powder, which has a cake-like appearance. POLIVY is supplied as:

Carton Contents | NDC
One 30 mg single-dose vial | NDC 50242-103-01
One 140 mg single-dose vial | NDC 50242-105-01

Storage and Handling

Store refrigerated at 2°C to 8°C (36°F to 46°F) in original carton to protect from light. Do not use beyond the expiration date shown on the carton. Do not freeze. Do not shake.

POLIVY is a hazardous drug. Follow applicable special handling and disposal procedures.^1

17 PATIENT COUNSELING INFORMATION

Peripheral Neuropathy

Advise patients that POLIVY can cause peripheral neuropathy. Advise patients to report to their healthcare provider any numbness or tingling of the hands or feet or any muscle weakness [see Warnings and Precautions (5.1)].

Infusion-Related Reactions

Advise patients to contact their healthcare provider if they experience signs and symptoms of infusion reactions, including fever, chills, rash, or breathing problems, within 24 hours of infusion [see Warnings and Precautions (5.2)].

Myelosuppression

Advise patients to report signs or symptoms of bleeding or infection immediately. Advise patients of the need for periodic monitoring of blood counts [see Warnings and Precautions (5.3)].

Infections

Advise patients to contact their healthcare provider if a fever of 38°C (100.4°F) or greater or other evidence of potential infection such as chills, cough, or pain on urination develops. Advise patients of the need for periodic monitoring of blood counts [see Warnings and Precautions (5.4)].

Progressive Multifocal Leukoencephalopathy

Advise patients to seek immediate medical attention for new or changes in neurological symptoms such as confusion, dizziness, or loss of balance; difficulty talking or walking; or changes in vision [see Warnings and Precautions (5.5)].

Tumor Lysis Syndrome

Advise patients to seek immediate medical attention for symptoms of tumor lysis syndrome such as nausea, vomiting, diarrhea, and lethargy [see Warnings and Precautions (5.6)].

Hepatotoxicity

Advise patients to report symptoms that may indicate liver injury, including fatigue, anorexia, right upper abdominal discomfort, dark urine, or jaundice [see Warnings and Precautions (5.7)].

Embryo-Fetal Toxicity

Advise females of reproductive potential of the potential risk to a fetus. Advise females to contact their healthcare provider if they become pregnant, or if pregnancy is suspected, during treatment with POLIVY [see Warnings and Precautions (5.8) and Use in Specific Populations (8.1)].

Females and Males of Reproductive Potential

Advise females of reproductive potential, and males with female partners of reproductive potential, to use effective contraception during treatment with POLIVY and for 3 months and 5 months after the last dose, respectively [see Use in Specific Populations (8.3)].

Lactation

Advise women not to breastfeed while receiving POLIVY and for 2 months after the last dose [see Use in Specific Populations (8.2)].

POLIVY® [polatuzumab vedotin-piiq]

Manufactured by:
Genentech, Inc.
A Member of the Roche Group
1 DNA Way
South San Francisco, CA 94080-4990

POLIVY is a registered trademark of Genentech, Inc.
© 2023 Genentech, Inc.

U.S. License No. 1048

Representative sample of labeling (see the HOW SUPPLIED section for complete listing):

PRINCIPAL DISPLAY PANEL - 140 mg Vial Carton

NDC 50242-105-01
Polivy®
(polatuzumab vedotin-piiq)
For Injection

140 mg per vial

For Intravenous Infusion Only.
Reconstitute and Dilute
prior to administration.
Single-Dose Vial.
Discard unused portion.

CAUTION: Hazardous Agent

Rx only

1 vial
Genentech

11007928

PRINCIPAL DISPLAY PANEL - 30 mg Vial Carton

NDC 50242-103-01
Polivy®
(polatuzumab vedotin-piiq)
For Injection

30 mg per vial

For Intravenous Infusion Only.
Reconstitute and Dilute
prior to administration.
Single-Dose Vial.
Discard unused portion.

CAUTION: Hazardous Agent

Rx only

1 vial
Genentech

11008718